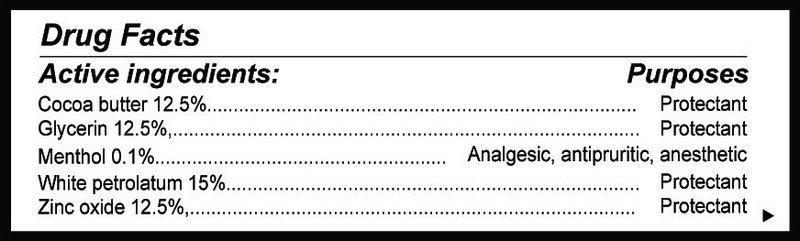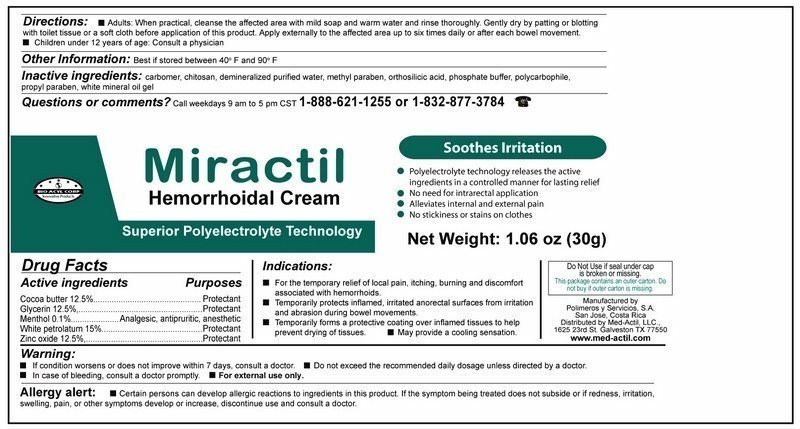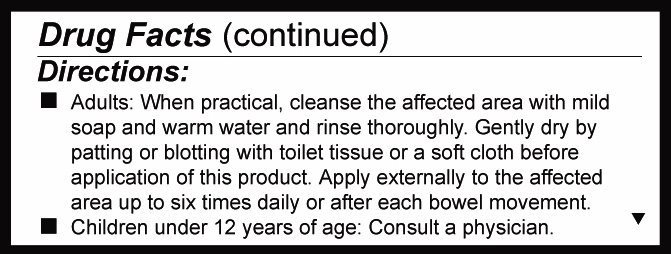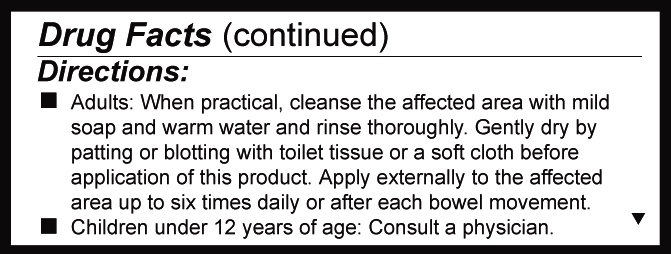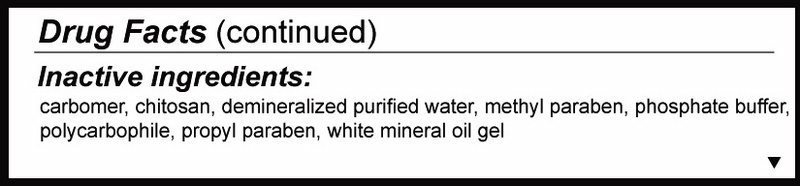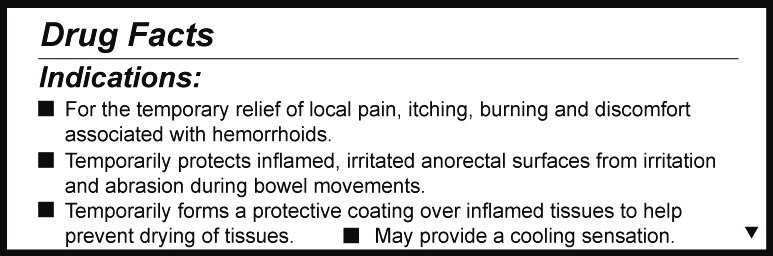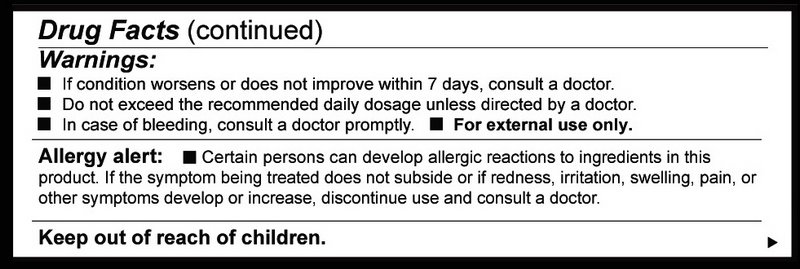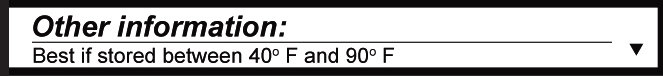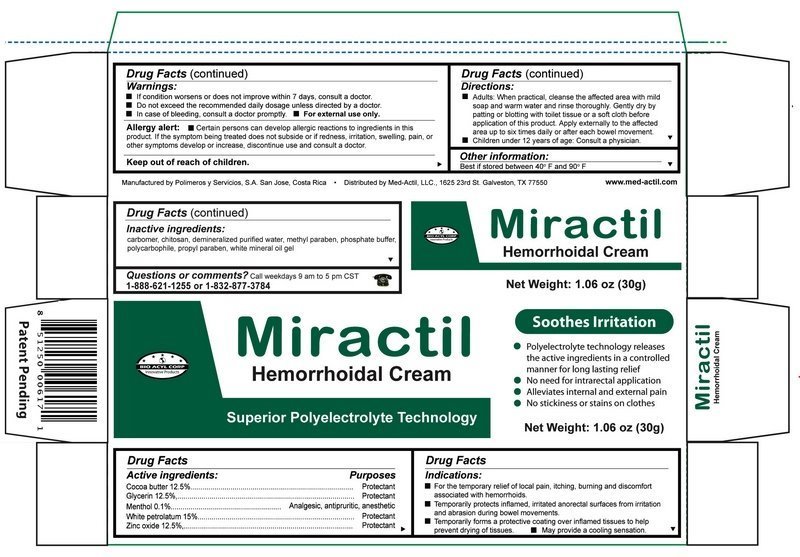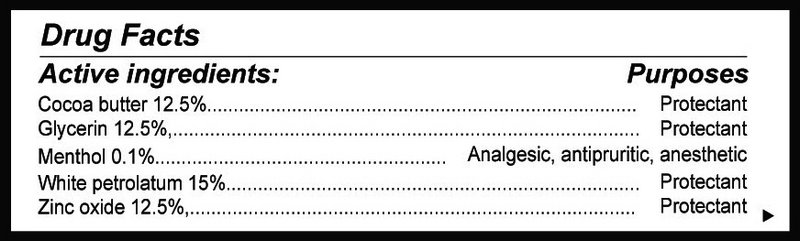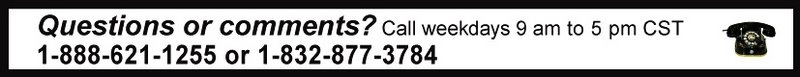 DRUG LABEL: MIRACTIL
NDC: 69492-011 | Form: GEL
Manufacturer: POLIMEROS Y SERVICIOS S.A-
Category: otc | Type: HUMAN OTC DRUG LABEL
Date: 20190305

ACTIVE INGREDIENTS: COCOA BUTTER 125 mg/1 g; GLYCERIN 125 mg/1 g; MENTHOL 1 mg/1 g; PETROLATUM 150 mg/1 g; ZINC OXIDE 125 mg/1 g
INACTIVE INGREDIENTS: CARBOXYPOLYMETHYLENE; CHITOSAN MEDIUM MOLECULAR WEIGHT (200-400 MPA.S); METHYLPARABEN; ORTHOSILICIC ACID; SODIUM PHOSPHATE, DIBASIC; POLYCARBOPHIL; PROPYLPARABEN; WATER; MINERAL OIL

Submission for Miractil Hemorrhoidal Cream

Detail showing Active Ingredient from package

Active ingredients.jpg

Information shown both on container label and paclage

Detail showing Inactive ingredient from package

Inactive ingredinets.jpg

Information shown both on cntainer label and package

Detail showing Purpose within Active Ingredients from package

Purpose.jpg

Information shown both on container label and package

Detail showing Indications from pacage

Indications.jpg

Information shown both on container label and package

Detail shyowing Instructions for use and named Directions from package

Directions.jpg

Information shown both on container label and package

Detail showing Dosage abd Administration within Directions from package

Dosage and administration.jpg

Information shown both on container lable and package

Detail showing Warnings from package

Warnings.jpg

Information shown both on container label and package

Detail showing Keep Out of Reach of Children within Warnings from package

Keep out of reavh of children.jpg

nformation shown on package

Detail showing Questions from package

Questions or comments.jpg

nformation shown both on container label and package

Detail showing Other Safety Information from package

Other information.jpg

Information shown both on container label and package

Representative sample image of carton/container label

Container label.jpg

General view of inner container label

Package content of labeling.jpg

General view of box content of labeling